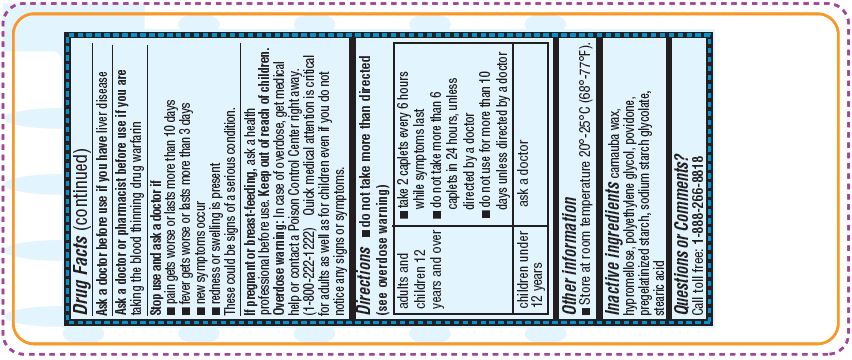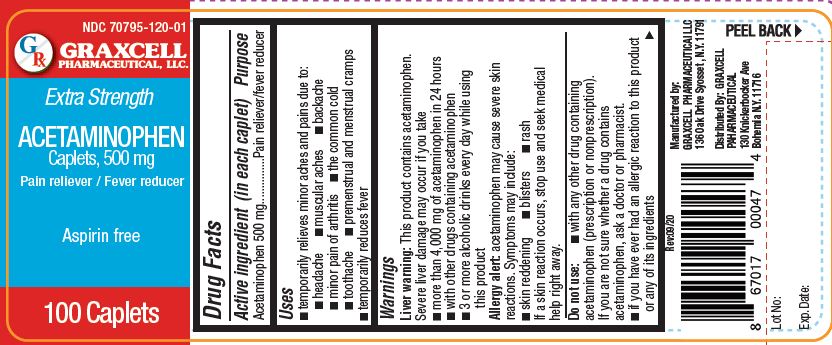 DRUG LABEL: ACETAMINOPHEN CAPLETS, 500 MG

NDC: 70795-1200 | Form: TABLET
Manufacturer: GRAXCELL PHARMACEUTICAL, LLC
Category: otc | Type: HUMAN OTC DRUG LABEL
Date: 20211221

ACTIVE INGREDIENTS: ACETAMINOPHEN 500 mg/1 1
INACTIVE INGREDIENTS: CARNAUBA WAX; HYPROMELLOSE 2208 (100000 MPA.S); POLYETHYLENE GLYCOL 1000; POVIDONE; STARCH, CORN; SODIUM STARCH GLYCOLATE TYPE A CORN; STEARIC ACID

Acetaminophen Caplets, 500 mg, 70795-1200

Active ingredient (in each tablet)

ACETAMINOPHEN 500 MG

Purpose

PAIN RELIEVER/FEVER REDUCER

USES

• temporarily relieves minor aches and pains due to:
• headache
• muscular aches
• backache
• minor pain of arthritis
• the common cold
• toothache
• premenstrual and menstrual cramps
• temporarily reduces fever

Warnings

Liver warning: This product contains acetaminophen. Severe liver damage may occur if you take

- more than 4,000 mg of acetaminophen in 24 hours
- with other drugs containing acetaminophen
- 3 or more alcoholic drinks every day while using this product

Allergy alert: acetaminophen may cause severe skin reactions. Symptoms may include:

- skin reddening
- blisters
- rash

If a skin reaction occurs, stop use and seek medical help right away.

Do not use:

- with any other drug containing acetaminophen (prescription or nonprescription). If you are not sure whether a drug contains acetaminophen, ask a doctor or pharmacist.
- you have ever had an allergic reaction to this productor any of its ingredients

Ask a doctor before use if you have liver disease

Ask a doctor or pharmacist before use if you are taking the blood thinning drug warfarin

Stop use and ask a doctor if

- pain gets worse or lasts more than 10 days
- fever gets worse or lasts more than 3 days
- new symptoms occur
- redness or swelling is present

These could be signs of a serious condition.

If pregnant or breast-feeding, ask a health professional before use.

Do not use

without consulting a physician

Ask a physician before use

if you have a sodium restricted diet due to multiple organ diseases

Stop use and ask a physician

If symptoms of heat cramps continue for more than 24 hours

If pregnant or breast-feeding

ask a health professional before use.

Keep out of reach of children.

In case of overdose, get medical help or contact a Poison Control Center right away

Keep out of reach of children.

Overdose warning: In case of overdose, get medical help or contact a Poison Control Center right away. (1-800-222-1222) Quick medical attention is critical for adults as well as for children even if you do not notice any signs or symptoms.

Directions

- do not take more than directed (see overdose warning)

Adults and children 12 years and over

- take 2 caplets every 6 hours while symptoms last
- do not take more than 6 caplets in 24 hours, unless directed by a doctor
- do not use for more than 10 days unless directed by a doctor

Children under 12 years

- ask a doctor

Other information

- Store at room temperature 20°-25°C (68°-77°F).

INACTIVE INGREDIENTS

carnauba wax, hypromellose, polyethylene glycol, povidone, pregelatinized starch, sodium starch glycolate, stearic acid